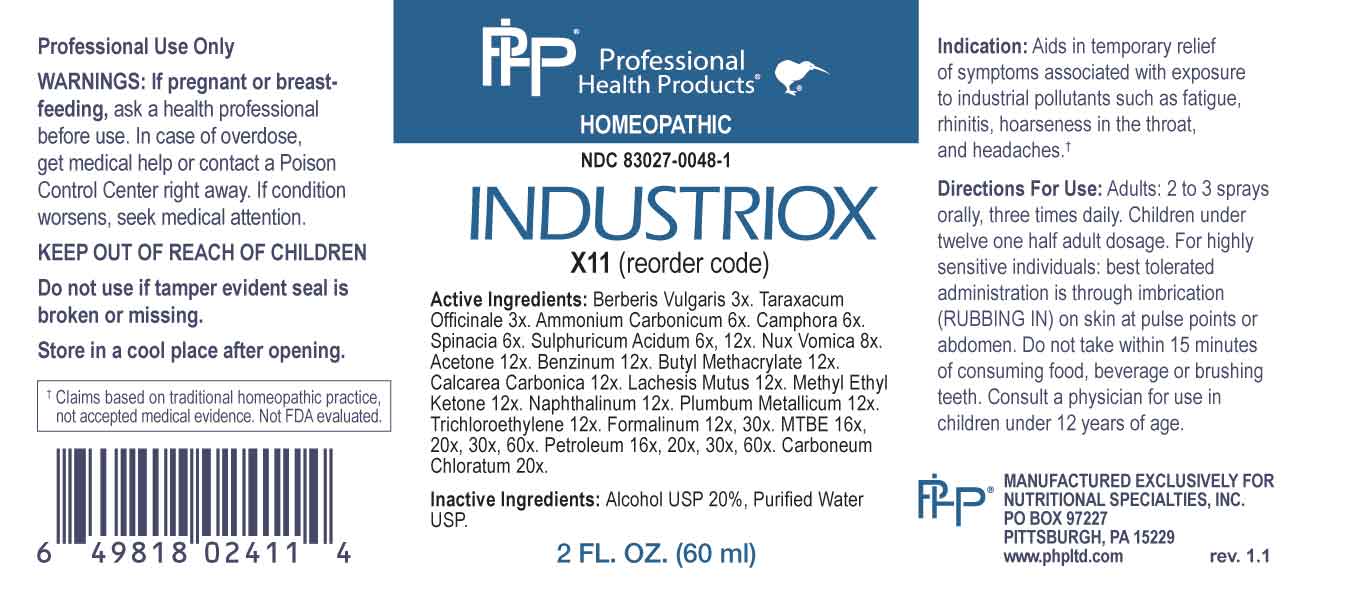 DRUG LABEL: Industriox
NDC: 83027-0048 | Form: SPRAY
Manufacturer: Nutritional Specialties, Inc.
Category: homeopathic | Type: HUMAN OTC DRUG LABEL
Date: 20230925

ACTIVE INGREDIENTS: BERBERIS VULGARIS ROOT BARK 3 [hp_X]/1 mL; TARAXACUM OFFICINALE 3 [hp_X]/1 mL; AMMONIUM CARBONATE 6 [hp_X]/1 mL; CAMPHOR (NATURAL) 6 [hp_X]/1 mL; SPINACIA OLERACEA ROOT 6 [hp_X]/1 mL; SULFURIC ACID 6 [hp_X]/1 mL; STRYCHNOS NUX-VOMICA SEED 8 [hp_X]/1 mL; ACETONE 12 [hp_X]/1 mL; BENZENE 12 [hp_X]/1 mL; N-BUTYL METHACRYLATE 12 [hp_X]/1 mL; OYSTER SHELL CALCIUM CARBONATE, CRUDE 12 [hp_X]/1 mL; LACHESIS MUTA VENOM 12 [hp_X]/1 mL; METHYL ETHYL KETONE 12 [hp_X]/1 mL; NAPHTHALENE 12 [hp_X]/1 mL; LEAD 12 [hp_X]/1 mL; TRICHLOROETHYLENE 12 [hp_X]/1 mL; FORMALDEHYDE SOLUTION 12 [hp_X]/1 mL; TERT-BUTYL METHYL ETHER 16 [hp_X]/1 mL; KEROSENE 16 [hp_X]/1 mL; CARBON TETRACHLORIDE 20 [hp_X]/1 mL
INACTIVE INGREDIENTS: WATER; ALCOHOL

DRUG FACTS:

ACTIVE INGREDIENTS:

Berberis Vulgaris 3X, Taraxacum Officinale 3X, Ammonium Carbonicum 6X, Camphora 6X, Spinacia 6X, Sulphuricum Acidum 6X, 12X, Nux Vomica 8X, Acetone 12X, Benzinum 12X, Butyl Methacrylate 12X, Calcarea Carbonica 12X, Lachesis Mutus 12X, Methyl Ethyl Ketone 12X, Naphthalinum 12X, Plumbum Metallicum 12X, Trichloroethylene 12X, Forlmalinum 12X, 30X, MTBE 16X, 20X, 30X, 60X, Petroleum 16X, 20X, 30X, 60X, Carboneum Chloratum 20X.

PURPOSE:

Aids in temporary relief of symptoms associated with exposure to industrial pollutants such as fatigue, rhinitis, hoarseness in the throat, and headaches.†

†Claims based on traditional homeopathic practice, not accepted medical evidence. Not FDA evaluated.

WARNINGS:

Professional Use Only

If pregnant or breast-feeding, ask a health professional before use.

In case of overdose, get medical help or contact a Poison Control Center right away.

If condition worsens, seek medical attention.

KEEP OUT OF REACH OF CHILDREN

Do not use if tamper evident seal is broken or missing.

Store in a cool place after opening

KEEP OUT OF REACH OF CHILDREN:

In case of overdose, get medical help or contact a Poison Control Center right away.

DIRECTIONS:

Adults: 2 to 3 sprays orally, three times daily. Children under twelve one half adult dosage. For highly sensitive individuals: best tolerated administration is through imbrication (RUBBING IN) on skin at pulse points or abdomen. Do not take within 15 minutes of consuming food, beverage or brushing teeth. Consult a physician for use in children under 12 years of age.

INDICATIONS:

Aids in temporary relief of symptoms associated with exposure to industrial pollutants such as fatigue, rhinitis, hoarseness in the throat, and headaches.†

†Claims based on traditional homeopathic practice, not accepted medical evidence. Not FDA evaluated.

INACTIVE INGREDIENTS:

Alcohol USP 20%, Purified Water USP.

QUESTIONS:

MANUFACTURED EXCLUSIVELY FOR

NUTRITIONAL SPECIALTIES, INC.

PO BOX 97227

PITTSBURG, PA 15229

www.phpltd.com

PACKAGE LABEL DISPLAY:

Professional

Health Products

HOMEOPATHIC

NDC 83027-0048-1

INDUSTRIOX

2 FL. OZ (60 ml)